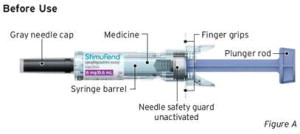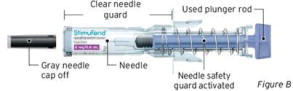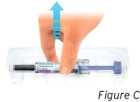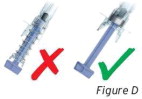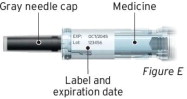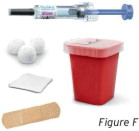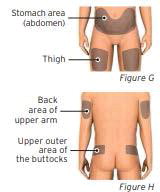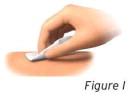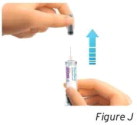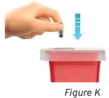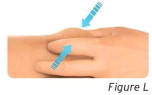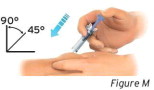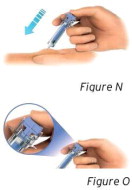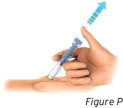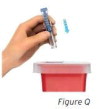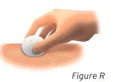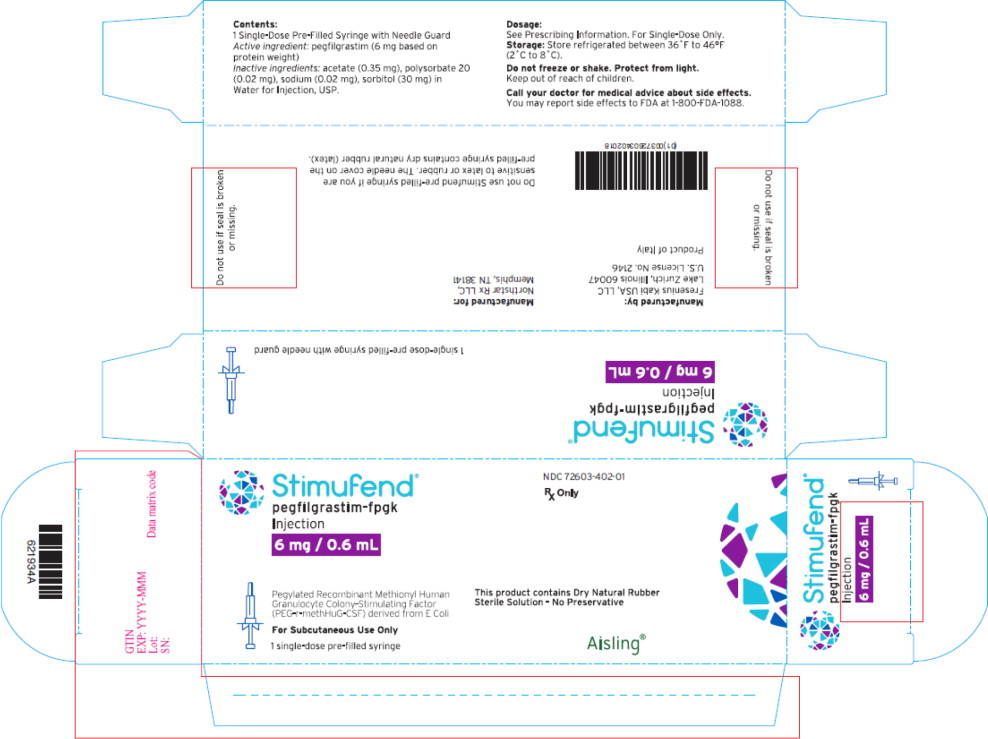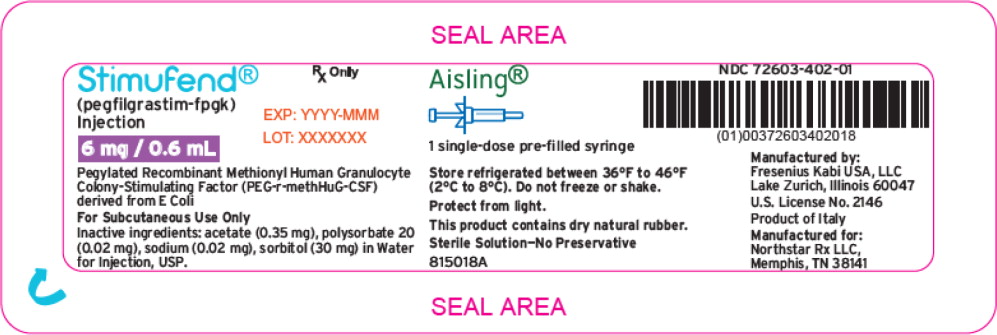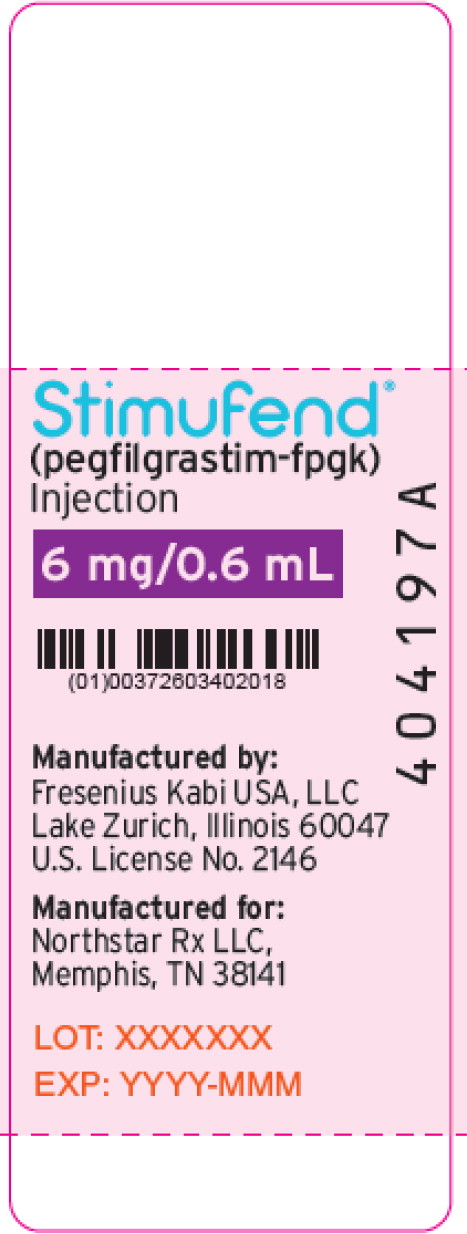 DRUG LABEL: STIMUFEND
NDC: 72603-402 | Form: INJECTION, SOLUTION
Manufacturer: NORTHSTAR RX LLC
Category: prescription | Type: HUMAN PRESCRIPTION DRUG LABEL
Date: 20251130

ACTIVE INGREDIENTS: PEGFILGRASTIM 6 mg/0.6 mL
INACTIVE INGREDIENTS: ACETATE ION; POLYSORBATE 20; SODIUM; SORBITOL; WATER

HIGHLIGHTS OF PRESCRIBING INFORMATION

These highlights do not include all the information needed to use STIMUFEND safely and effectively. See full prescribing information for STIMUFEND.
STIMUFEND® (pegfilgrastim-fpgk) injection, for subcutaneous use
Initial U.S. Approval: 2022
STIMUFEND (pegfilgrastim-fpgk) is biosimilar [Biosimilar means that the biological product is approved based on data demonstrating that it is highly similar to an FDA-approved biological product, known as a reference product, and that there are no clinically meaningful differences between the biosimilar product and the reference product. Biosimilarity of Stimufend has been demonstrated for the condition(s) of use (e.g. indication(s), dosing regimen(s), strength(s), dosage form(s), and route(s) of administration described in its Full Prescribing Information.] to NEULASTA (pegfilgrastim)

RECENT MAJOR CHANGES

Indications and Usage, Patients with Hematopoietic Subsyndrome of Acute Radiation Syndrome (1.2) | 9/2023
Dosage and Administration, Patients with Hematopoietic Subsyndrome of Acute Radiation Syndrome (2.2) | 9/2023

1 INDICATIONS AND USAGE

Stimufend is a leukocyte growth factor indicated to

- decrease the incidence of infection, as manifested by febrile neutropenia, in patients with non-myeloid malignancies receiving myelosuppressive anti-cancer drugs associated with a clinically significant incidence of febrile neutropenia. (1.1)
- Increase survival in patients acutely exposed to myelosuppressive doses of radiation (Hematopoietic Subsyndrome of Acute Radiation Syndrome). (1.2)

Limitations of Use

Stimufend is not indicated for the mobilization of peripheral blood progenitor cells for hematopoietic stem cell transplantation.

2 DOSAGE AND ADMINISTRATION

- Patients with cancer receiving myelosuppressive chemotherapy
  - 6 mg administered subcutaneously once per chemotherapy cycle. (2.1)
  - Do not administer between 14 days before and 24 hours after administration of cytotoxic chemotherapy. (2.1)
  - Use weight-based dosing for pediatric patients weighing less than 45 kg; refer to Table 1. (2.3)
- Patients acutely exposed to myelosuppressive doses of radiation
  - Two doses, 6 mg each, administered subcutaneously one week apart. Administer the first dose as soon as possible after suspected or confirmed exposure to myelosuppressive doses of radiation, and a second dose one week after. (2.2)
  - Use weight-based dosing for pediatric patients weighing less than 45 kg; refer to Table 1. (2.3)

3 DOSAGE FORMS AND STRENGTHS

Injection: 6 mg/0.6 mL solution in a single-dose pre-filled syringe for manual use only. (3)

4 CONTRAINDICATIONS

Patients with a history of serious allergic reactions to human granulocyte colony-stimulating factors such as pegfilgrastim products or filgrastim products. (4)

5 WARNINGS AND PRECAUTIONS

- Fatal splenic rupture: Evaluate patients who report left upper abdominal or shoulder pain for an enlarged spleen or splenic rupture. (5.1)
- Acute respiratory distress syndrome (ARDS): Evaluate patients who develop fever, lung infiltrates, or respiratory distress. Discontinue Stimufend in patients with ARDS. (5.2)
- Serious allergic reactions, including anaphylaxis: Permanently discontinue Stimufend in patients with serious allergic reactions. (5.3)
- Fatal sickle cell crises: Discontinue Stimufend if sickle cell crisis occurs. (5.4)
- Glomerulonephritis: Evaluate and consider dose- reduction or interruption of Stimufend if causality is likely. (5.5)
- Thrombocytopenia: Monitor platelet counts. (5.7)
- Myelodysplastic Syndrome (MDS) and Acute Myeloid Leukemia (AML): Monitor patients with breast and lung cancer using Stimufend in conjunction with chemotherapy and/or radiotherapy for signs and symptoms of MDS/AML. (5.10)

6 ADVERSE REACTIONS

Most common adverse reactions (≥ 5% difference in incidence compared to placebo) are bone pain and pain in extremity. (6.1)

To report SUSPECTED ADVERSE REACTIONS, contact Northstar Rx LLC at 1-800-206-7821 or FDA at 1-800-FDA-1088 or www.fda.gov/medwatch.

FULL PRESCRIBING INFORMATION

1 INDICATIONS AND USAGE

1.1 Patients with Cancer Receiving Myelosuppressive Chemotherapy

Stimufend is indicated to decrease the incidence of infection, as manifested by febrile neutropenia, in patients with non-myeloid malignancies receiving myelosuppressive anti-cancer drugs associated with a clinically significant incidence of febrile neutropenia [see Clinical Studies (14.1)].

Limitations of Use

Stimufend is not indicated for the mobilization of peripheral blood progenitor cells for hematopoietic stem cell transplantation.

1.2 Patients with Hematopoietic Subsyndrome of Acute Radiation Syndrome

Stimufend is indicated to increase survival in patients acutely exposed to myelosuppressive doses of radiation [see Dosage and Administration (2.2) and Clinical Studies (14.2)].

2 DOSAGE AND ADMINISTRATION

2.1 Patients with Cancer Receiving Myelosuppressive Chemotherapy

The recommended dosage of Stimufend is a single subcutaneous injection of 6 mg administered once per chemotherapy cycle. For dosing in pediatric patients weighing less than 45 kg, refer to Table 1. Do not administer Stimufend between 14 days before and 24 hours after administration of cytotoxic chemotherapy.

2.2 Patients with Hematopoietic Subsyndrome of Acute Radiation Syndrome

The recommended dose of Stimufend is two doses, 6 mg each, administered subcutaneously one week apart. For dosing in pediatric patients weighing less than 45 kg, refer to Table 1. Administer the first dose as soon as possible after suspected or confirmed exposure to radiation levels greater than 2 gray (Gy). Administer the second dose one week after the first dose.

Obtain a baseline complete blood count (CBC). Do not delay administration of Stimufend if a CBC is not readily available. Estimate a patient's absorbed radiation dose (i.e., level of radiation exposure) based on information from public health authorities, biodosimetry if available, or clinical findings such as time to onset of vomiting or lymphocyte depletion kinetics.

2.3 Administration

Stimufend is administered subcutaneously via a single-dose prefilled syringe for manual use.

Prior to use, remove the carton from the refrigerator and allow the Stimufend prefilled syringe to reach room temperature for a minimum of 30 minutes. Discard any prefilled syringe left at room temperature for greater than 72 hours.

Parenteral drug products should be inspected visually for particulate matter and discoloration prior to administration, whenever solution and container permit. Do not administer Stimufend if discoloration or particulates are observed.

The needle cap on the pre-filled syringes contains dry natural rubber (derived from latex); persons with latex allergies should not administer these products.

Pediatric Patients weighing less than 45 kg

The Stimufend pre-filled syringe is not designed to allow for direct administration of doses less than 0.6 mL (6 mg). The syringe does not bear graduation marks, which are necessary to accurately measure doses of Stimufend less than 0.6 mL (6 mg) for direct administration to patients. Thus, the direct administration to patients requiring dosing of less than 0.6 mL (6 mg) is not recommended due to the potential for dosing errors. Refer to Table 1.

Table 1. Dosing of Stimufend for Pediatric Patients Weighing Less Than 45 kg
Body Weight | Stimufend Dose | Volume to Administer
Less than 10 kg* | See below* | See below*
10 - 20 kg | 1.5 mg | 0.15 mL
21 - 30 kg | 2.5 mg | 0.25 mL
31 - 44 kg | 4 mg | 0.4 mL
*For pediatric patients weighing less than 10 kg, administer 0.1 mg/kg (0.01 mL/kg) of Stimufend.

3 DOSAGE FORMS AND STRENGTHS

Stimufend is a clear, colorless, preservative-free solution available as:

- Injection: 6 mg/0.6 mL in a single-dose pre-filled syringe for manual use only.

4 CONTRAINDICATIONS

Stimufend is contraindicated in patients with a history of serious allergic reactions to pegfilgrastim products or filgrastim products. Reactions have included anaphylaxis [see Warnings and Precautions (5.3)].

5 WARNINGS AND PRECAUTIONS

5.1 Splenic Rupture

Splenic rupture, including fatal cases, can occur following the administration of pegfilgrastim products. Evaluate for an enlarged spleen or splenic rupture in patients who report left upper abdominal or shoulder pain after receiving Stimufend.

5.2 Acute Respiratory Distress Syndrome

Acute respiratory distress syndrome (ARDS) can occur in patients receiving pegfilgrastim products. Evaluate patients who develop fever and lung infiltrates or respiratory distress after receiving Stimufend for ARDS. Discontinue Stimufend in patients with ARDS.

5.3 Serious Allergic Reactions

Serious allergic reactions, including anaphylaxis, can occur in patients receiving pegfilgrastim products. The majority of reported events occurred upon initial exposure. Allergic reactions, including anaphylaxis, can recur within days after the discontinuation of initial anti-allergic treatment. Permanently discontinue Stimufend in patients with serious allergic reactions. Do not administer Stimufend to patients with a history of serious allergic reactions to pegfilgrastim products or filgrastim products.

5.4 Use in Patients with Sickle Cell Disorders

Severe and sometimes fatal sickle cell crises can occur in patients with sickle cell disorders receiving pegfilgrastim products. Discontinue Stimufend if sickle cell crisis occurs.

5.5 Glomerulonephritis

Glomerulonephritis has occurred in patients receiving pegfilgrastim products. The diagnoses were based upon azotemia, hematuria (microscopic and macroscopic), proteinuria, and renal biopsy.

Generally, events of glomerulonephritis resolved after dose-reduction or discontinuation of pegfilgrastim products. If glomerulonephritis is suspected, evaluate for cause. If causality is likely, consider dose- reduction or interruption of Stimufend.

5.6 Leukocytosis

White blood cell (WBC) counts of 100 x 10^9/L or greater have been observed in patients receiving pegfilgrastim products. Monitoring of complete blood count (CBC) during Stimufend therapy is recommended.

5.7 Thrombocytopenia

Thrombocytopenia has been reported in patients receiving pegfilgrastim products. Monitor platelet counts.

5.8 Capillary Leak Syndrome

Capillary leak syndrome has been reported after G-CSF administration, including pegfilgrastim products, and is characterized by hypotension, hypoalbuminemia, edema and hemoconcentration. Episodes vary in frequency, severity and may be life-threatening if treatment is delayed. Patients who develop symptoms of capillary leak syndrome should be closely monitored and receive standard symptomatic treatment, which may include a need for intensive care.

5.9 Potential for Tumor Growth Stimulatory Effects on Malignant Cells

The granulocyte colony-stimulating factor (G-CSF) receptor through which pegfilgrastim products and filgrastim products act has been found on tumor cell lines. The possibility that pegfilgrastim products act as a growth factor for any tumor type, including myeloid malignancies and myelodysplasia, diseases for which pegfilgrastim products are not approved, cannot be excluded.

5.10 Myelodysplastic Syndrome (MDS) and Acute Myeloid Leukemia (AML) in Patients with Breast and Lung Cancer

MDS and AML have been associated with the use of pegfilgrastim products in conjunction with chemotherapy and/or radiotherapy in patients with breast and lung cancer. Monitor patients for signs and symptoms of MDS/AML in these settings.

5.11 Aortitis

Aortitis has been reported in patients receiving pegfilgrastim products. It may occur as early as the first week after start of therapy. Manifestations may include generalized signs and symptoms such as fever, abdominal pain, malaise, back pain, and increased inflammatory markers (e.g., c-reactive protein and white blood cell count). Consider aortitis in patients who develop these signs and symptoms without known etiology. Discontinue Stimufend if aortitis is suspected.

5.12 Nuclear Imaging

Increased hematopoietic activity of the bone marrow in response to growth factor therapy has been associated with transient positive bone imaging changes. This should be considered when interpreting bone imaging results.

6 ADVERSE REACTIONS

The following clinically significant adverse reactions are discussed in greater detail in other sections of the labeling:

- Splenic Rupture [see Warnings and Precautions (5.1)]
- Acute Respiratory Distress Syndrome [see Warnings and Precautions (5.2)]
- Serious Allergic Reactions [see Warnings and Precautions (5.3)]
- Use in Patients with Sickle Cell Disorders [see Warnings and Precautions (5.4)]
- Glomerulonephritis [see Warnings and Precautions (5.5)]
- Leukocytosis [see Warnings and Precautions (5.6)]
- Thrombocytopenia [see Warnings and Precautions (5.7)]
- Capillary Leak Syndrome [see Warnings and Precautions (5.8)]
- Potential for Tumor Growth Stimulatory Effects on Malignant Cells [see Warnings and Precautions (5.9)]
- Myelodysplastic syndrome [see Warnings and Precautions (5.10)]
- Acute myeloid leukemia [see Warnings and Precautions (5.10)]
- Aortitis [see Warnings and Precautions (5.11)]

6.1 Clinical Trials Experience

Because clinical trials are conducted under widely varying conditions, adverse reaction rates observed in the clinical trials of a drug cannot be directly compared with rates in the clinical trials of another drug and may not reflect the rates observed in clinical practice.

Pegfilgrastim clinical trials safety data are based upon 932 patients receiving pegfilgrastim in seven randomized clinical trials. The population was 21 to 88 years of age and 92% female. The ethnicity was 75% Caucasian, 18% Hispanic, 5% Black, and 1% Asian. Patients with breast (n = 823), lung and thoracic tumors (n = 53) and lymphoma (n = 56) received pegfilgrastim after nonmyeloablative cytotoxic chemotherapy. Most patients received a single 100 mcg/kg (n = 259) or a single 6 mg (n = 546) dose per chemotherapy cycle over 4 cycles.

The following adverse reaction data in Table 2 are from a randomized, double-blind, placebo-controlled study in patients with metastatic or non-metastatic breast cancer receiving docetaxel 100 mg/m^2 every 21 days (Study 3). A total of 928 patients were randomized to receive either 6 mg pegfilgrastim (n = 467) or placebo (n = 461). The patients were 21 to 88 years of age and 99% female. The ethnicity was 66% Caucasian, 31% Hispanic, 2% Black, and < 1% Asian, Native American, or other.

The most common adverse reactions occurring in ≥ 5% of patients and with a between-group difference of ≥ 5% higher in the pegfilgrastim arm in placebo-controlled clinical trials are bone pain and pain in extremity.

Table 2. Adverse Reactions with ≥ 5% Higher Incidence in Pegfilgrastim Patients Compared to Placebo in Study 3
Body System Adverse Reaction | Placebo (N = 461) | Pegfilgrastim 6 mg SC on Day 2 (N = 467)
Musculoskeletal and connective tissue disorders
Bone pain | 26% | 31%
Pain in extremity | 4% | 9%

Leukocytosis

In clinical studies, leukocytosis (WBC counts > 100 x 10^9/L) was observed in less than 1% of 932 patients with non-myeloid malignancies receiving pegfilgrastim. No complications attributable to leukocytosis were reported in clinical studies.

6.2 Immunogenicity

As with all therapeutic proteins, there is potential for immunogenicity. The detection of antibody formation is highly dependent on the sensitivity and specificity of the assay. Additionally, the observed incidence of antibody (including neutralizing antibody) positivity in an assay may be influenced by several factors, including assay methodology, sample handling, timing of sample collection, concomitant medications, and underlying disease. For these reasons, comparison of the incidence of antibodies in the studies described below with the incidence of antibodies in other studies or to other pegfilgrastim products may be misleading.

Binding antibodies to pegfilgrastim were detected using a BIAcore assay. The approximate limit of detection for this assay is 500 ng/mL. Pre-existing binding antibodies were detected in approximately 6% (51/849) of patients with metastatic breast cancer. Four of 521 pegfilgrastim-treated subjects who were negative at baseline developed binding antibodies to pegfilgrastim following treatment. None of these 4 patients had evidence of neutralizing antibodies detected using a cell-based bioassay.

6.3 Postmarketing Experience

The following adverse reactions have been identified during post approval use of pegfilgrastim products. Because these reactions are reported voluntarily from a population of uncertain size, it is not always possible to reliably estimate their frequency or establish a causal relationship to drug exposure.

- Splenic rupture and splenomegaly (enlarged spleen) [see Warnings and Precautions (5.1)]
- Acute respiratory distress syndrome (ARDS) [see Warnings and Precautions (5.2)]
- Allergic reactions/hypersensitivity, including anaphylaxis, skin rash, urticaria, generalized erythema, and flushing [see Warnings and Precautions (5.3)]
- Sickle cell crisis [see Warnings and Precautions (5.4)]
- Glomerulonephritis [see Warnings and Precautions (5.5)]
- Leukocytosis [see Warnings and Precautions (5.6)]
- Thrombocytopenia [see Warnings and Precautions (5.7)]
- Capillary Leak Syndrome [see Warnings and Precautions (5.8)]
- Injection site reactions
- Sweet's syndrome (acute febrile neutrophilic dermatosis), cutaneous vasculitis
- Myelodysplastic syndrome (MDS) and acute myeloid leukemia (AML) in patients with breast and lung cancer receiving chemotherapy and/or radiotherapy [see Warnings and Precautions (5.10)]
- Aortitis [see Warnings and Precautions (5.11)]
- Alveolar hemorrhage

8 USE IN SPECIFIC POPULATIONS

8.1 Pregnancy

Risk Summary

Although available data with Stimufend or pegfilgrastim product use in pregnant women are insufficient to establish whether there is a drug associated risk of major birth defects, miscarriage, or adverse maternal or fetal outcomes, there are available data from published studies in pregnant women exposed to filgrastim products. These studies have not established an association of filgrastim product use during pregnancy with major birth defects, miscarriage, or adverse maternal or fetal outcomes.

In animal studies, no evidence of reproductive/developmental toxicity occurred in the offspring of pregnant rats that received cumulative doses of pegfilgrastim approximately 10 times the recommended human dose (based on body surface area). In pregnant rabbits, increased embryolethality and spontaneous abortions occurred at 4 times the maximum recommended human dose simultaneously with signs of maternal toxicity (see Data).

The estimated background risk of major birth defects and miscarriage for the indicated population is unknown. All pregnancies have a background risk of birth defect, loss, or other adverse outcomes.

In the U.S. general population, the estimated background risks of major birth defects and miscarriage in clinically recognized pregnancies is 2-4% and 15-20%, respectively.

Data

Animal Data

Pregnant rabbits were dosed with pegfilgrastim subcutaneously every other day during the period of organogenesis. At cumulative doses ranging from the approximate human dose to approximately 4 times the recommended human dose (based on body surface area), the treated rabbits exhibited decreased maternal food consumption, maternal weight loss, as well as reduced fetal body weights and delayed ossification of the fetal skull; however, no structural anomalies were observed in the offspring from either study. Increased incidences of post-implantation losses and spontaneous abortions (more than half the pregnancies) were observed at cumulative doses approximately 4 times the recommended human dose, which were not seen when pregnant rabbits were exposed to the recommended human dose.

Three studies were conducted in pregnant rats dosed with pegfilgrastim at cumulative doses up to approximately 10 times the recommended human dose at the following stages of gestation: during the period of organogenesis, from mating through the first half of pregnancy, and from the first trimester through delivery and lactation. No evidence of fetal loss or structural malformations was observed in any study. Cumulative doses equivalent to approximately 3 and 10 times the recommended human dose resulted in transient evidence of wavy ribs in fetuses of treated mothers (detected at the end of gestation but no longer present in pups evaluated at the end of lactation).

8.2 Lactation

Risk Summary

There are no data on the presence of pegfilgrastim products in human milk, the effects on the breastfed child, or the effects on milk production. Other filgrastim products are secreted poorly into breast milk, and filgrastim products are not absorbed orally by neonates. The developmental and health benefits of breastfeeding should be considered along with the mother's clinical need for Stimufend and any potential adverse effects on the breastfed child from Stimufend or from the underlying maternal condition.

8.4 Pediatric Use

The safety and effectiveness of Stimufend have been established in pediatric patients. No overall differences in safety were identified between adult and pediatric patients based on postmarketing surveillance and review of the scientific literature.

Use of Stimufend in pediatric patients for chemotherapy-induced neutropenia is based on Stimufend's approval as a biosimilar to pegfilgrastim and evidence from adequate and well-controlled studies of pegfilgrastim in adults with additional pharmacokinetic and safety data of pegfilgrastim in pediatric patients with sarcoma [see Clinical Pharmacology (12.3) and Clinical Studies (14.1)].

The use of Stimufend to increase survival in pediatric patients acutely exposed to myelosuppressive doses of radiation is based on Stimufend's approval as a biosimilar to pegfilgrastim, evidence from efficacy studies of pegfilgrastim conducted in animals, and clinical data supporting the use of pegfilgrastim in patients with cancer receiving myelosuppressive chemotherapy. Efficacy studies of pegfilgrastim products could not be conducted in humans with acute radiation syndrome for ethical and feasibility reasons. Results from population modeling and simulation indicate that two weight-based doses of pegfilgrastim (Table 1) administered one week apart provide pediatric patients weighing less than 45 kg with exposures comparable to that of adults receiving two 6 mg doses one week apart [see Dosage and Administration (2.3), Clinical Pharmacology (12.3) and Clinical Studies (14.2)].

8.5 Geriatric Use

Of the 932 patients with cancer who received pegfilgrastim in clinical studies, 139 (15%) were aged 65 and over, and 18 (2%) were aged 75 and over. No overall differences in safety or effectiveness were observed between patients aged 65 and older and younger patients.

10 OVERDOSAGE

Overdosage of pegfilgrastim may result in leukocytosis and bone pain. Events of edema, dyspnea, and pleural effusion have been reported in a single patient who administered pegfilgrastim on 8 consecutive days in error. In the event of overdose, the patient should be monitored for adverse reactions [see Adverse Reactions (6)].

11 DESCRIPTION

Pegfilgrastim-fpgk is a covalent conjugate of recombinant methionyl human G-CSF and monomethoxypolyethylene glycol. Recombinant methionyl human G-CSF is a water-soluble 175 amino acid protein with a molecular weight of approximately 19 kilodaltons (kD). Recombinant methionyl human G-CSF is obtained from the bacterial fermentation of a strain of E coli transformed with a genetically engineered plasmid containing the human G-CSF gene. To produce pegfilgrastim-fpgk, a 20 kD monomethoxypolyethylene glycol molecule is covalently bound to the N-terminal methionyl residue of recombinant methionyl human G-CSF. The average molecular weight of pegfilgrastim-fpgk is approximately 39 kD.

Stimufend (pegfilgrastim-fpgk) injection is supplied in 0.6 mL pre-filled syringes for manual subcutaneous injection. The pre-filled syringe does not bear graduation marks and is designed to deliver the entire contents of the syringe (6 mg/0.6 mL).

The delivered 0.6 mL dose from the prefilled syringe contains 6 mg pegfilgrastim-fpgk (based on protein weight) in a sterile, clear, colorless, preservative-free solution (pH 4.0) containing acetate (0.35 mg), polysorbate 20 (0.02 mg), sodium (0.02 mg), and sorbitol (30 mg) in Water for Injection, USP.

12 CLINICAL PHARMACOLOGY

12.1 Mechanism of Action

Pegfilgrastim products are colony-stimulating factors that act on hematopoietic cells by binding to specific cell surface receptors, thereby stimulating proliferation, differentiation, commitment, and end cell functional activation.

12.2 Pharmacodynamics

Animal data and clinical data in humans suggest a correlation between pegfilgrastim products' exposure and the duration of severe neutropenia as a predictor of efficacy. Selection of the dosing regimen of Stimufend is based on reducing the duration of severe neutropenia.

12.3 Pharmacokinetics

The pharmacokinetics of pegfilgrastim was studied in 379 patients with cancer. The pharmacokinetics of pegfilgrastim was nonlinear, and clearance decreased with increases in dose. Neutrophil receptor binding is an important component of the clearance of pegfilgrastim, and serum clearance is directly related to the number of neutrophils. In addition to numbers of neutrophils, body weight appeared to be a factor. Patients with higher body weights experienced higher systemic exposure to pegfilgrastim after receiving a dose normalized for body weight. A large variability in the pharmacokinetics of pegfilgrastim was observed. The half-life of pegfilgrastim ranged from 15 to 80 hours after subcutaneous injection.

Specific Populations

No gender-related differences were observed in the pharmacokinetics of pegfilgrastim, and no differences were observed in the pharmacokinetics of geriatric patients (≥ 65 years of age) compared with younger patients (< 65 years of age) [see Use in Specific Populations (8.5)].

Renal Impairment

In a study of 30 subjects with varying degrees of renal dysfunction, including end stage renal disease, renal dysfunction had no effect on the pharmacokinetics of pegfilgrastim.

Pediatric Patients with Cancer Receiving Myelosuppressive Chemotherapy

The pharmacokinetics and safety of pegfilgrastim were studied in 37 pediatric patients with sarcoma in Study 4 [see Clinical Studies (14.1)]. The mean (± standard deviation [SD]) systemic exposure (AUC0-inf) of pegfilgrastim after subcutaneous administration at 100 mcg/kg was 47.9 (± 22.5) mcg·hr/mL in the youngest age group (0 to 5 years, n = 11), 22.0 (± 13.1) mcg·hr/mL in the 6 to 11 years age group (n = 10), and 29.3 (± 23.2) mcg·hr/mL in the 12 to 21 years age group (n = 13). The terminal elimination half- lives of the corresponding age groups were 30.1 (± 38.2) hours, 20.2 (± 11.3) hours, and 21.2 (± 16.0) hours, respectively.

Patients Acutely Exposed to Myelosuppressive Doses of Radiation

The pharmacokinetics of pegfilgrastim products is not available in patients acutely exposed to myelosuppressive doses of radiation. Based on limited pharmacokinetic data in irradiated non-human primates, the area under the concentration-time curve (AUC), reflecting the exposure to pegfilgrastim in non-human primates following a 300 mcg/kg dose of pegfilgrastim, appears to be greater than in humans receiving a 6 mg dose. Results from population modeling and simulation indicate that two 6 mg doses of pegfilgrastim administered one week apart in adults result in clinically relevant effects on duration of grade 3 and 4 neutropenia. In addition, weight-based dosing in pediatric patients weighing less than 45 kg [see Dosage and Administration, Section 2.3, Table 1] provides exposures comparable to those in adults receiving two 6 mg doses one week apart.

13 NONCLINICAL TOXICOLOGY

13.1 Carcinogenesis, Mutagenesis, Impairment of Fertility

No carcinogenicity or mutagenesis studies have been performed with pegfilgrastim products.

Pegfilgrastim did not affect reproductive performance or fertility in male or female rats at cumulative weekly doses approximately 6 to 9 times higher than the recommended human dose (based on body surface area).

14 CLINICAL STUDIES

14.1 Patients with Cancer Receiving Myelosuppressive Chemotherapy

Pegfilgrastim was evaluated in three randomized, double-blind, controlled studies. Studies 1 and 2 were active-controlled studies that employed doxorubicin 60 mg/m^2 and docetaxel 75 mg/m^2 administered every 21 days for up to 4 cycles for the treatment of metastatic breast cancer. Study 1 investigated the utility of a fixed dose of pegfilgrastim. Study 2 employed a weight-adjusted dose. In the absence of growth factor support, similar chemotherapy regimens have been reported to result in a 100% incidence of severe neutropenia (ANC < 0.5 x 10^9/L) with a mean duration of 5 to 7 days and a 30% to 40% incidence of febrile neutropenia. Based on the correlation between the duration of severe neutropenia and the incidence of febrile neutropenia found in studies with filgrastim, duration of severe neutropenia was chosen as the primary endpoint in both studies, and the efficacy of pegfilgrastim was demonstrated by establishing comparability to filgrastim-treated patients in the mean days of severe neutropenia.

In Study 1, 157 patients were randomized to receive a single subcutaneous injection of pegfilgrastim (6 mg) on day 2 of each chemotherapy cycle or daily subcutaneous filgrastim (5 mcg/kg/day) beginning on day 2 of each chemotherapy cycle. In Study 2, 310 patients were randomized to receive a single subcutaneous injection of pegfilgrastim (100 mcg/kg) on day 2 or daily subcutaneous filgrastim (5 mcg/kg/day) beginning on day 2 of each chemotherapy cycle.

Both studies met the major efficacy outcome measure of demonstrating that the mean days of severe neutropenia of pegfilgrastim-treated patients did not exceed that of filgrastim-treated patients by more than 1 day in cycle 1 of chemotherapy. The mean days of cycle 1 severe neutropenia in Study 1 were 1.8 days in the pegfilgrastim arm compared to 1.6 days in the filgrastim arm [difference in means 0.2 (95% CI - 0.2, 0.6)] and in Study 2 were 1.7 days in the pegfilgrastim arm compared to 1.6 days in the filgrastim arm [difference in means 0.1 (95% CI - 0.2, 0.4)].

A secondary endpoint in both studies was days of severe neutropenia in cycles 2 through 4 with results similar to those for cycle 1.

Study 3 was a randomized, double-blind, placebo-controlled study that employed docetaxel 100 mg/m^2 administered every 21 days for up to 4 cycles for the treatment of metastatic or non-metastatic breast cancer. In this study, 928 patients were randomized to receive a single subcutaneous injection of pegfilgrastim (6 mg) or placebo on day 2 of each chemotherapy cycle. Study 3 met the major trial outcome measure of demonstrating that the incidence of febrile neutropenia (defined as temperature ≥ 38.2°C and ANC ≤ 0.5 x 10^9/L) was lower for pegfilgrastim-treated patients as compared to placebo-treated patients (1% versus 17%, respectively, p < 0.001). The incidence of hospitalizations (1% versus 14%) and IV anti-infective use (2% versus 10%) for the treatment of febrile neutropenia was also lower in the pegfilgrastim-treated patients compared to the placebo-treated patients.

Study 4 was a multicenter, randomized, open-label study to evaluate the efficacy, safety, and pharmacokinetics [see Clinical Pharmacology (12.3)] of pegfilgrastim in pediatric and young adult patients with sarcoma. Patients with sarcoma receiving chemotherapy age 0 to 21 years were eligible. Patients were randomized to receive subcutaneous pegfilgrastim as a single-dose of 100 mcg/kg (n = 37) or subcutaneous filgrastim at a dose 5 mcg/kg/day (n = 6) following myelosuppressive chemotherapy. Recovery of neutrophil counts was similar in the pegfilgrastim and filgrastim groups. The most common adverse reaction reported was bone pain.

14.2 Patients with Hematopoietic Subsyndrome of Acute Radiation Syndrome

Efficacy studies of pegfilgrastim products could not be conducted in humans with acute radiation syndrome for ethical and feasibility reasons. Approval of this indication was based on efficacy studies conducted in animals and data supporting pegfilgrastim's effect on severe neutropenia in patients with cancer receiving myelosuppressive chemotherapy [see Dosage and Administration (2.1)].

The recommended dose of Stimufend is two doses, 6 mg each, administered one week apart for humans exposed to myelosuppressive doses of radiation. For pediatric patients weighing less than 45 kg, dosing of Stimufend is weight-based and is provided in Table 1 [see Dosage and Administration (2.3)]. This dosing regimen is based on population modeling and simulation analyses. The exposure associated with this dosing regimen is expected to provide sufficient pharmacodynamic activity to treat humans exposed to myelosuppressive doses of radiation [see Clinical Pharmacology (12.3)]. The safety of pegfilgrastim at a dose of 6 mg has been assessed on the basis of clinical experience in patients with cancer receiving myelosuppressive chemotherapy.

The efficacy of pegfilgrastim for the acute radiation syndrome setting was studied in a randomized, placebo-controlled non-human primate model of radiation injury. Rhesus macaques were randomized to either a control (n = 23) or treated (n = 23) cohort. On study day 0, animals (n = 6 to 8 per irradiation day) were exposed to total body irradiation (TBI) of 7.50 ± 0.15 Gy delivered at 0.8 ± 0.03 Gy/min, representing a dose that would be lethal in 50% of animals by 60 days of follow-up (LD50/60). Animals were administered subcutaneous injections of a blinded treatment (control article [5% dextrose in water] or pegfilgrastim [300-319 mcg/kg/day]) on study day 1 and on study day 8. The primary endpoint was survival. Animals received medical management consisting of intravenous fluids, antibiotics, blood transfusions, and other support as required.

Pegfilgrastim significantly (at 0.0014 level of significance) increased 60-day survival in irradiated non-human primates: 91% survival (21/23) in the pegfilgrastim group compared to 48% survival (11/23) in the control group.

16 HOW SUPPLIED/STORAGE AND HANDLING

Stimufend single-dose prefilled syringe for manual use

Stimufend (pegfilgrastim-fpgk) injection is a clear, colorless, preservative-free solution supplied in a pre-filled single-dose syringe for manual use containing 6 mg pegfilgrastim-fpgk, supplied with a 27-gauge, 1/2-inch needle with a Safe'n'Sound® passive Needle Guard.

The needle cap of the pre-filled syringe contains natural rubber (a derivative of latex).

Stimufend is provided in a dispensing pack containing one sterile 6 mg/0.6 mL pre-filled syringe (NDC 72603-402-01).

Stimufend pre-filled syringe does not bear graduation marks and is intended only to deliver the entire contents of the syringe (6 mg/0.6 mL) for direct administration. Use of the pre-filled syringe is not recommended for direct administration for pediatric patients weighing less than 45 kg who require doses that are less than the full contents of the syringe.

Store refrigerated between 36°F to 46°F (2°C to 8°C) in the carton to protect from light. Do not shake. Discard syringes stored at room temperature for more than 72 hours. Do not freeze. Discard syringe if frozen.

17 PATIENT COUNSELING INFORMATION

Advise the patient to read the FDA-approved patient labeling (Patient Information and Instructions for Use). Advise patients of the following risks and potential risks with Stimufend:

- Splenic rupture and splenomegaly
- Acute Respiratory Distress Syndrome
- Serious allergic reactions
- Sickle cell crisis
- Glomerulonephritis
- Increased risk of Myelodysplastic Syndrome and/or Acute Myeloid Leukemia in patients with breast and lung cancer who receive Stimufend in conjunction with chemotherapy and/or radiation therapy
- Capillary Leak Syndrome
- Aortitis

Advise patients acutely exposed to myelosuppressive doses of radiation (Hematopoietic Subsyndrome of Acute Radiation Syndrome) that efficacy studies of pegfilgrastim products for this indication could not be conducted in humans for ethical and feasibility reasons and that, therefore, approval of this use was based on efficacy studies conducted in animals [see Clinical Studies (14.2)].

Instruct patients who self-administer Stimufend using the single-dose pre-filled syringe of the:

- Importance of following the Instructions for Use (see Instructions for Use).
- Dangers of reusing syringes.
- Importance of following local requirements for proper disposal of used syringes.

Manufactured by:
Fresenius Kabi USA, LLC
Lake Zurich, Illinois 60047
U.S. License No. 2146
Product of Italy

Manufactured for:
Northstar Rx LLC,
Memphis, TN 38141

PATIENT INFORMATION

Patient Information Stimufend® (STIM-yu-fend) (pegfilgrastim-fpgk) injection
Single-Dose Prefilled Syringe

What is Stimufend?
Stimufend is a man-made form of granulocyte colony-stimulating factor (G-CSF). G-CSF is a substance produced by the body. It stimulates the growth of neutrophils, a type of white blood cell important in the body's fight against infection.
Acute Radiation Syndrome: The effectiveness of pegfilgrastim for this use was only studied in animals, because it could not be studied in people.

Do not take Stimufend if you have had a serious allergic reaction to pegfilgrastim products or filgrastim products.

Before you receive Stimufend, tell your healthcare provider about all of your medical conditions, including if you:

- have a sickle cell disorder.
- have kidney problems.
- are allergic to latex. The needle cap on the prefilled syringe contains dry natural rubber (derived from latex). You should not give Stimufend using the prefilled syringe if you have latex allergies.
- are pregnant or plan to become pregnant. It is not known if Stimufend will harm your unborn baby.
- are breastfeeding or plan to breastfeed. It is not known if Stimufend passes into your breast milk.

Tell your healthcare provider about all of the medicines you take, including prescription and over-the-counter medicines, vitamins, and herbal supplements.

How will I receive Stimufend?

- Stimufend is given as an injection under your skin (subcutaneous injection) by a healthcare provider. If your healthcare provider decides that the subcutaneous injections can be given at home by you or your caregiver, follow the detailed “Instructions for Use” that comes with your Stimufend for information on how to prepare and inject a dose of Stimufend.
- You and your caregiver will be shown how to prepare and inject Stimufend before you use it.
- You should not inject a dose of Stimufend to children weighing less than 45 kg from a Stimufend prefilled syringe. A dose less than 0.6 mL (6 mg) cannot be accurately measured using the Stimufend prefilled syringe.
- If you are receiving Stimufend because you are also receiving chemotherapy, the last dose of Stimufend should be injected at least 14 days before and 24 hours after your dose of chemotherapy.
- If you miss a dose of Stimufend, talk to your healthcare provider about when you should give your next dose.

What are possible side effects of Stimufend?
Stimufend may cause serious side effects, including:

- Spleen rupture. Your spleen may become enlarged and can rupture. A ruptured spleen can cause death. Call your healthcare provider right away if you have pain in the left upper stomach area or your left shoulder.
- A serious lung problem called Acute Respiratory Distress Syndrome (ARDS). Call your healthcare provider or get emergency help right away if you have shortness of breath with or without a fever, trouble breathing, or a fast rate of breathing.
- Serious allergic reactions. Stimufend can cause serious allergic reactions. These reactions can cause a rash over your whole body, shortness of breath, wheezing, dizziness, swelling around your mouth or eyes, fast heart rate, and sweating. If you have any of these symptoms, stop using Stimufend and call your healthcare provider or get emergency medical help right away.
- Sickle cell crises. You may have a serious sickle cell crisis, which could lead to death, if you have a sickle cell disorder and receive Stimufend. Call your healthcare provider right away if you have symptoms of sickle cell crisis such as pain or difficulty breathing.
- Kidney injury (glomerulonephritis). Stimufend can cause kidney injury. Call your healthcare provider right away if you develop any of the following symptoms:
  - swelling of your face or ankles
  - blood in your urine or dark colored urine
  - you urinate less than usual
- Increased white blood cell count (leukocytosis). Your healthcare provider will check your blood during treatment with Stimufend.
- Decreased platelet count (thrombocytopenia). Your healthcare provider will check your blood during treatment with Stimufend. Tell your healthcare provider if you have unusual bleeding or bruising during treatment with Stimufend. This could be a sign of decreased platelet counts, which may reduce the ability of your blood to clot.
- Capillary Leak Syndrome. Stimufend can cause fluid to leak from blood vessels into your body's tissues. This condition is called “Capillary Leak Syndrome” (CLS). CLS can quickly cause you to have symptoms that may become life-threatening. Get emergency medical help right away if you develop any of the following symptoms:
  - swelling or puffiness and are urinating less than usual
  - trouble breathing
  - swelling of your stomach area (abdomen) and feeling of fullness
  - dizziness or feeling faint
  - a general feeling of tiredness
- Myelodysplastic syndrome and acute myeloid leukemia. If you have breast cancer or lung cancer, when Stimufend is used with chemotherapy and radiation therapy, or with radiation therapy alone, you may have an increased risk of developing a precancerous blood condition called myelodysplastic syndrome (MDS) or a blood cancer called acute myeloid leukemia (AML). Symptoms may include tiredness, fever, and easy bruising or bleeding. Call your healthcare provider if you develop these symptoms during treatment with Stimufend.
- Inflammation of the aorta (aortitis). Inflammation of the aorta (the large blood vessel which transports blood from the heart to the body) has been reported in patients who received pegfilgrastim products. Symptoms may include fever, abdominal pain, feeling tired, and back pain. Call your healthcare provider if you experience these symptoms.

The most common side effects of Stimufend are pain in the bones, arms, and legs.
These are not all the possible side effects of Stimufend. Call your healthcare provider for medical advice about side effects. You may report side effects to FDA at 1-800-FDA-1088.

How should I store Stimufend?

- Store Stimufend in the refrigerator between 36°F to 46°F (2°C to 8°C).
- Do not freeze. Throw away (dispose of) Stimufend that has been frozen.
- Keep the prefilled syringe in the original carton to protect from light or physical damage.
- Do not shake the prefilled syringe.
- Take Stimufend out of the refrigerator 30 minutes before use and allow it to reach room temperature before preparing an injection.
- Throw away (dispose of) any Stimufend that has been left at room temperature, 68°F to 77°F (20°C to 25°C), for more than 72 hours.

Keep the Stimufend prefilled syringe out of the reach of children.

General information about the safe and effective use of Stimufend.
Medicines are sometimes prescribed for purposes other than those listed in a Patient Information leaflet. Do not use Stimufend for a condition for which it was not prescribed. Do not give Stimufend to other people, even if they have the same symptoms that you have. It may harm them. You can ask your pharmacist or healthcare provider for information about Stimufend that is written for health professionals.

What are the ingredients in Stimufend?
Active ingredient: pegfilgrastim-fpgk
Inactive ingredients: acetate, polysorbate 20, sodium and sorbitol in Water for Injection, USP.

Manufactured by:
Fresenius Kabi USA, LLC
Lake Zurich, Illinois 60047
U.S. License No. 2146
Product of Italy
Manufactured for:
Northstar Rx LLC,
Memphis, TN 38141
For more information go to www.northstarrxllc.com or call 1-800-206-7821.

This Patient Information has been approved by the U.S. Food and Drug Administration.

Revised: August 2025

451860A

Instructions for Use
STIMUFEND® (STIM-yu-fend)

(pegfilgrastim-fpgk)
Injection, for subcutaneous use

Single-Dose Prefilled Syringe

Guide to parts

After Use (Clear needle guard locked in place)

Important: The needle is covered by a gray needle cap before use.

Important:

Read the Patient Information for important information you need to know about STIMUFEND before using these Instructions for Use.

Before you use a STIMUFEND prefilled syringe, read this important information.

Storing the prefilled syringe

- Store STIMUFEND in the refrigerator between 36°F to 46°F (2°C to 8°C).
- Do not freeze. Throw away (dispose of) STIMUFEND that has been frozen.
- Keep the prefilled syringe in the original carton to protect from light or physical damage.
- Take the prefilled syringe out of the refrigerator 30 minutes before use and allow it to reach room temperature before preparing an injection.
- Throw away (dispose of) any STIMUFEND that has been left at room temperature, 68°F to 77°F (20°C to 25°C), for more than 72 hours.
- Keep the STIMUFEND prefilled syringe out of the reach of children.

Using the prefilled syringe

- It is important that you do not try to give the injection unless you or your caregiver has received training from your healthcare provider.
- Make sure the name STIMUFEND appears on the carton and prefilled syringe label.
- Check the carton and prefilled syringe label to make sure the dose strength is 6 mg/0.6 mL.
- You should not inject a dose of STIMUFEND to children weighing less than 45 kg from a STIMUFEND prefilled syringe. A dose less than 0.6 mL (6 mg) cannot be accurately measured using the STIMUFEND prefilled syringe.
- Do not use a prefilled syringe after the expiration date on the label.
- Do not shake the prefilled syringe.
- Do not remove the gray needle cap from the prefilled syringe until you are ready to inject.
- Do not use the prefilled syringe if the carton is open or damaged.
- Do not use a prefilled syringe if it has been dropped on a hard surface. The prefilled syringe may be broken even if you cannot see the break. Use a new prefilled syringe.
- The gray needle cap on the prefilled syringe contains dry natural rubber (made from latex). Tell your healthcare provider if you are allergic to latex. You should not give STIMUFEND using the prefilled syringe if you have latex allergies.
  The prefilled syringe has a clear needle guard that automatically activates to cover the needle after the injection is given. Do not use a prefilled syringe if the clear needle guard has been activated. Use another prefilled syringe that has not been activated and is ready to use.

Call your healthcare provider if you have any questions.

Step 1: Prepare

1.1 Remove the prefilled syringe carton from the refrigerator. Remove the syringe tray from the carton.

On a clean, well-lit surface, place the syringe tray at room temperature for 30 minutes before you give an injection.

- Do not use the prefilled syringe if the carton is damaged.
- Do not try to warm the prefilled syringe by using a heat source such as hot water or microwave.
- Do not leave the prefilled syringe in direct sunlight.
- Do not shake the prefilled syringe.

Open the tray by peeling away the cover. Grab the clear needle guard to remove the prefilled syringe from the tray (see Figure C).

For safety reasons:

- Do not grab the plunger rod.
- Do not grab the gray needle cap.

1.2 Inspect the medicine and prefilled syringe.

Make sure the medicine in the prefilled syringe is clear and colorless.

- Do not use the prefilled syringe if:
  - The needle safety guard is activated (see Figure D).
  - The medicine is cloudy or discolored, or contains flakes or particles (see Figure E).
  - Any part appears cracked or broken.
  - The prefilled syringe has been dropped.
  - The gray needle cap is missing or not securely attached (see Figure E).
  - The expiration date printed on the label has passed (see Figure E).

In all cases use a new syringe and call your healthcare provider.

1.3 Gather all materials needed for the injection (see Figure F). Wash your hands thoroughly with soap and water.

On a clean, well-lit work surface, place the:

- Prefilled syringe
- Alcohol wipe
- Cotton ball or gauze pad
- Adhesive bandage
- Sharps disposal container

Step 2: Get ready

2.1 Prepare and clean the injection site(s). You can use:

- Stomach area (abdomen) except for a 2-inch area away from the navel (belly button) (see Figure G)
- Thigh (see Figure G)

- Back area of upper arm (only if someone else is giving you the injection) (see Figure H)
- Upper outer area of the buttocks (only if someone else is giving you the injection) (see Figure H)

Clean the injection site with an alcohol wipe (see Figure I). Let the skin dry.

- Do not touch this area again before injecting.
- If you want to use the same injection site, make sure it is not the same spot on the injection site you used for a previous injection.
- Do not inject into areas where the skin is tender, bruised, red, or hard. Avoid injecting into areas with scars or stretch marks.

2.2 Hold the prefilled syringe by the clear needle guard. Carefully pull the gray needle cap straight off and away from the body (see Figure J).

- Do not remove the gray needle cap from the prefilled syringe until you are ready to inject.
- Do not twist or bend the gray needle cap.
- Do not hold the prefilled syringe by the plunger rod.
- Do not put the gray needle cap back onto the prefilled syringe.

Important: Throw the gray needle cap into the sharps disposal container (see Figure K).

Step 3: Subcutaneous (under the skin) injection

3.1 Pinch the injection site to create a firm surface (see Figure L).

Important: Keep skin pinched while injecting.

3.2 Hold the pinch. Insert the needle into the skin at 45 to 90 degrees (see Figure M).

3.3 Using slow and constant pressure, push the plunger rod until it reaches the bottom (see Figure N).

- The plunger rod must be pushed down fully to ensure the full dose has been injected (see Figure O).
- Do not remove the needle from the skin when the plunger reaches the end and proceed with next step.

Step 4: Finish

4.1 Slowly release your thumb upward. This will allow the needle to move up into the clear needle guard and cover the entire needle (see Figure P).

- Do not try to recap the needle as it could lead to needle stick injury.

Important: When you remove the syringe, if it looks like the medicine is still in the syringe barrel, this means you have not received a full dose. Call your healthcare provider right away.

4.2 Discard (throw away) your prefilled syringe.

- Put the used prefilled syringe in a FDA-cleared sharps disposal container right away after use (see Figure Q).
- Do not throw away (dispose of) the prefilled syringe in your household trash.
- If you do not have a FDA-cleared sharps disposal container, you may use a household container that is:
  - made of a heavy-duty plastic,
  - can be closed with a tight-fitting, puncture-resistant lid, without sharps being able to come out,
  - upright and stable during use,
  - leak-resistant, and
  - properly labeled to warn of hazardous waste inside the container.

- When your sharps disposal container is almost full, you will need to follow your community guidelines for the right way to dispose of your sharps disposal container. There may be state or local laws about how you should throw away used needles and syringes. For more information about safe sharps disposal, and for specific information about sharps disposal in the state that you live in, go to the FDA's website at: http://www.fda.gov/safesharpsdisposal
- Do not reuse the prefilled syringe.
- Do not recycle the prefilled syringe or sharps disposal container or throw them in the household trash.

Important: Always keep the sharps disposal container out of the reach of children.

4.3 Examine the injection site.

- If there is blood, press a cotton ball or gauze pad on the injection site. Do not rub the injection site. Apply an adhesive bandage if needed (see Figure R).

This Instructions for Use has been approved by the U.S. Food and Drug Administration.

Manufactured by: Fresenius Kabi USA, LLC Lake Zurich, Illinois 60047

U.S. License No. 2146

Manufactured for: Northstar Rx LLC, Memphis, TN 38141

Revised: 8/2025

PACKAGE LABEL

PACKAGE LABEL – PRINCIPAL DISPLAY – STIMUFEND –One 0.6 mL Single-Dose

Prefilled Syringe CARTON PANEL

Stimufend

pegfilgrastim-fpgk

Injection

6 mg/0.6 mL

NDC 72603-402-01

Rx Only

Pegylated Recombinant Methionyl Human Granulocyte Colony-Stimulating Factor (PEG-rmethHuG-

CSF) derived from E Coli

For Subcutaneous Use Only

1 single-dose pre-filled syringe

This product contains Dry Natural Rubber

Sterile Solution-No Preservative

Aisling®

PACKAGE LABEL

PACKAGE LABEL – PRINCIPAL DISPLAY – STIMUFEND – 0.6 mL Single-Dose

Prefilled Syringe BLISTER PACK LABEL

Stimufend

(pegfilgrastim-fpgk)

Injection

6 mg/0.6 mL

Pegylated Recombinant Methionyl Human Granulocyte Colony-Stimulating Factor (PEG-rmethHuG-

CSF) derived from E Coli

For Subcutaneous Use Only

Inactive ingredients: acetate (0.35 mg), polysorbate 20

(0.02 mg), sodium (0.02 mg), sorbitol (30 mg) in Water

for Injection, USP.

Aisling®

1 single-dose pre-filled syringe

Store refrigerated between 36°F to 46°F (2°C to 8°C).

Do not freeze or shake.

Protect from light.

This product contains dry natural rubber.

Sterile Solution-No Preservative

815018A

NDC 72603-402-01

Manufactured by:

Fresenius Kabi USA, LLC

Lake Zurich, Illinois 60047

U.S. License No. 2146

Product of Italy

Manufactured for:

Northstar Rx LLC,

Memphis, TN 38141

PACKAGE LABEL

PACKAGE LABEL – PRINCIPAL DISPLAY – STIMUFEND – 0.6 mL Single-Dose

Prefilled SYRINGE LABEL

Stimufend

(pegfilgrastim-fpgk)

Injection

6 mg/0.6 mL

Manufactured by:

Fresenius Kabi USA, LLC

Lake Zurich, Illinois 60047

U.S. License No. 2146

Manufactured for:

Northstar Rx LLC,

Memphis, TN 38141

404197A